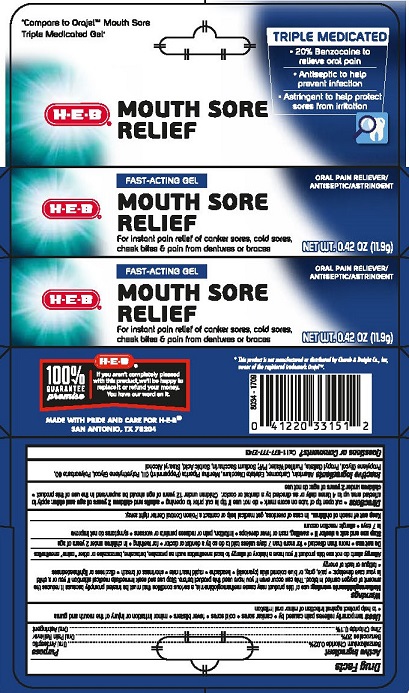 DRUG LABEL: HEB Mouth Sore Relief
NDC: 37808-312 | Form: GEL
Manufacturer: HEB
Category: otc | Type: HUMAN OTC DRUG LABEL
Date: 20230111

ACTIVE INGREDIENTS: BENZOCAINE 20 g/100 g; BENZALKONIUM CHLORIDE 0.02 g/100 g; ZINC CHLORIDE 0.1 g/100 g
INACTIVE INGREDIENTS: PROPYLENE GLYCOL; POLYSORBATE 60; ALLANTOIN; POLYETHYLENE GLYCOL 400; SACCHARIN SODIUM; SORBIC ACID; PEPPERMINT OIL; CARBOXYMETHYLCELLULOSE SODIUM, UNSPECIFIED FORM; EDETATE DISODIUM; POVIDONE, UNSPECIFIED; PROPYL GALLATE; WATER; STEARYL ALCOHOL

HEB Mouth Sore Relief Triple Med Gel

Drug Facts

Active ingredient

Benzalkonium chloride 0.02%

Benzocaine 20%

Zinc chloride 0.1%

Purpose

Oral Antiseptic

Oral Pain Reliever

Oral Astringent

Uses

temporarily relieves of pain caused by:

- canker sores
- cold sores
- fever blisters
- minor irritation of the mouth and gums
- to help protect against infection in minor oral irritation

Warnings

Methemoglobinemia warning: use of this product may cause methemoglobinemia, a serious condition that must be treated promptly because it reduces the amount of oxygen carried in the blood. This can occur even if you have used this product before. Stop use and seek immediate medical attention if you or a child in your care develops:

- pale, gray or blue colored skin (cyanosis)
- headache
- rapid heart rate
- shortness of breath
- dizziness or lightheadedness
- fatigue or lack of energy

Allergy alert: do not use this product if you have a history of allergy to local anesthetics such as procaine, butacaine, benzocaine or other “caine” anesthetics

Do not use

- more than directed
- for more than 7 days unless told to do so by a dentist or doctor
- for teething
- in children under 2 years of age

Stop use and ask a doctor if

- swelling, rash, fever develops
- irritation, pain or redness persist or worsen
- sore mouth symptoms do not improve in 7 days
- allergic reaction occurs

Keep out of reach of children. In case of overdose, get medical help or contact a Poison Control Center right away.

Directions

- cut open tip of tube on score mark
- adults and children 2 years of age and older: apply to affected area up to 4 times daily or as directed by a dentist or doctor.
- children under 12 years of age should be supervised in the use of this product.
- children under 2 years of age: do not use

INACTIVE INGREDIENT

Inactive ingredients Allantoin,Carbomer, Edetate Disodium, Mentha Piperata (Peppermint Oil), Polyethylene Glycol, Polysorbate 60, Propylene Glycol, Propyl Gallate, Purified Water, PVP, Sodium Saccharin, Sorbic Acid, Stearyl Alcohol.

Questions or Comments? Call 1-877-777-2473

MADE WITH PRIDE AND CARE FOR H-E-B®

SAN ANTONIO, TX 78204

PACKAGE LABEL

H-E-B

MOUTH SORE RELIEF

FAST-ACTING GEL

TRIPLE MEDICATED

ORAL PAIN RELIEVER/ANTISEPTIC/ASTRINGENT

NET WT 0.42 OZ (11.9 g)